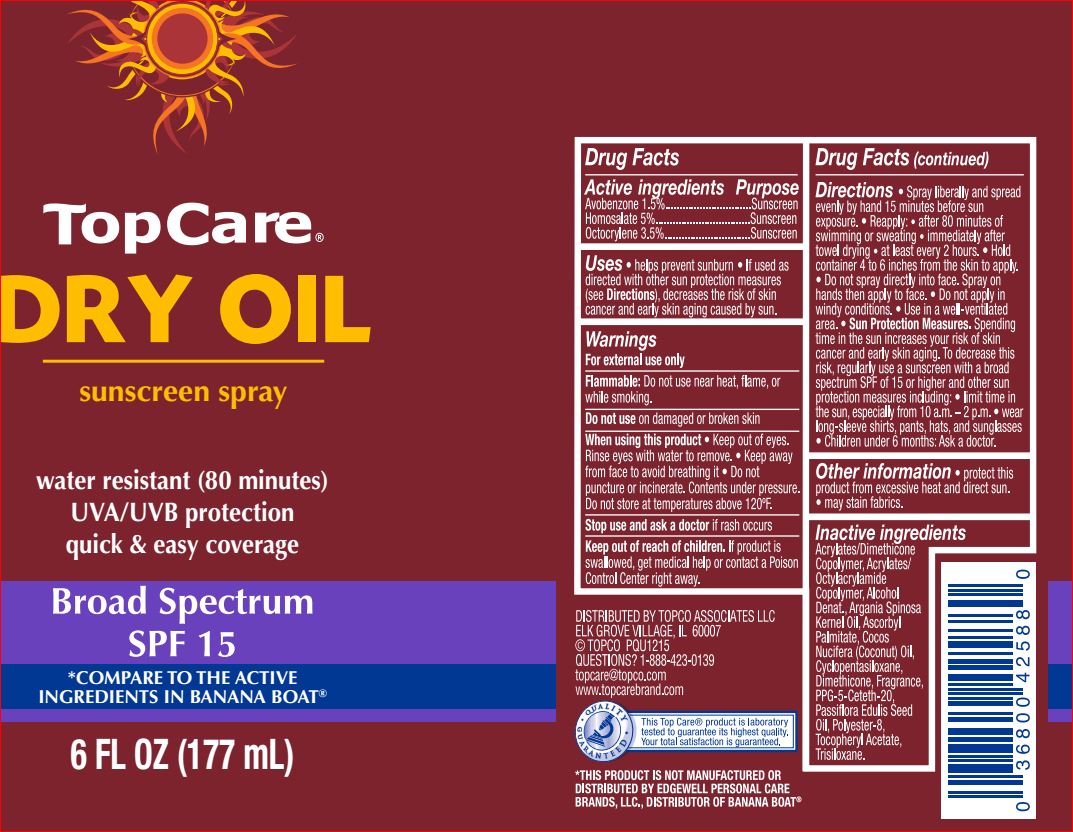 DRUG LABEL: Dry Oil SPF 15
NDC: 36800-731 | Form: SPRAY
Manufacturer: Top Care
Category: otc | Type: HUMAN OTC DRUG LABEL
Date: 20180718

ACTIVE INGREDIENTS: Avobenzone 1.5 g/100 g; Homosalate 5 g/100 g; Octocrylene 3.5 g/100 g
INACTIVE INGREDIENTS: ALCOHOL; ARGAN OIL; Ascorbyl Palmitate; COCONUT OIL; CYCLOMETHICONE 5; Dimethicone; PPG-5-Ceteth-20; Passiflora Edulis Seed Oil; POLYESTER-8 (1400 MW, CYANODIPHENYLPROPENOYL CAPPED); .ALPHA.-TOCOPHEROL ACETATE; Trisiloxane

Drug Facts

Active ingredients Purpose
Avobenzone 1.5%..............................Sunscreen
Homosalate 5%.................................Sunscreen
Octocrylene 3.5%..............................Sunscreen

INDICATIONS AND USAGE

Uses • helps prevent sunburn • If used as
directed with other sun protection measures
(see Directions), decreases the risk of skin
cancer and early skin aging caused by sun

Warnings
For external use only
Flammable: Do not use near heat, flame, or
while smoking.
Do not use on damaged or broken skin
When using this product • Keep out of eyes.
Rinse eyes with water to remove. • Keep away
from face to avoid breathing it • Do not
puncture or incinerate. Contents under pressure.
Do not store at temperatures above 120ºF.
Stop use and ask a doctor if rash occurs

Keep out of reach of children. If product is swallowed, get medical help or contact a Poison Control Center right away

Directions

• Spray liberally and spread
evenly by hand 15 minutes before sun
exposure. • Reapply: • after 80 minutes of
swimming or sweating • immediately after
towel drying • at least every 2 hours. • Hold
container 4 to 6 inches from the skin to apply.
• Do not spray directly into face. Spray on
hands then apply to face. • Do not apply in
windy conditions. • Use in a well-ventilated
area. • Sun Protection Measures. Spending
time in the sun increases your risk of skin
cancer and early skin aging. To decrease this
risk, regularly use a sunscreen with a broad
spectrum SPF of 15 or higher and other sun
protection measures including: • limit time in
the sun, especially from 10 a.m. – 2 p.m. • wear
long-sleeve shirts, pants, hats, and sunglasses
• Children under 6 months: Ask a doctor.

Other information

• protect this
product from excessive heat and direct sun.
• may stain fabrics.

Inactive ingredients
Acrylates/Dimethicone
Copolymer, Acrylates/
Octylacrylamide
Copolymer, Alcohol
Denat., Argania Spinosa
Kernel Oil, Ascorbyl
Palmitate, Cocos
Nucifera (Coconut) Oil,
Cyclopentasiloxane,
Dimethicone, Fragrance,
PPG-5-Ceteth-20,
Passiflora Edulis Seed
Oil, Polyester-8,
Tocopheryl Acetate,
Trisiloxane.